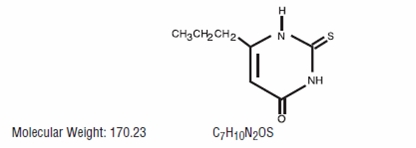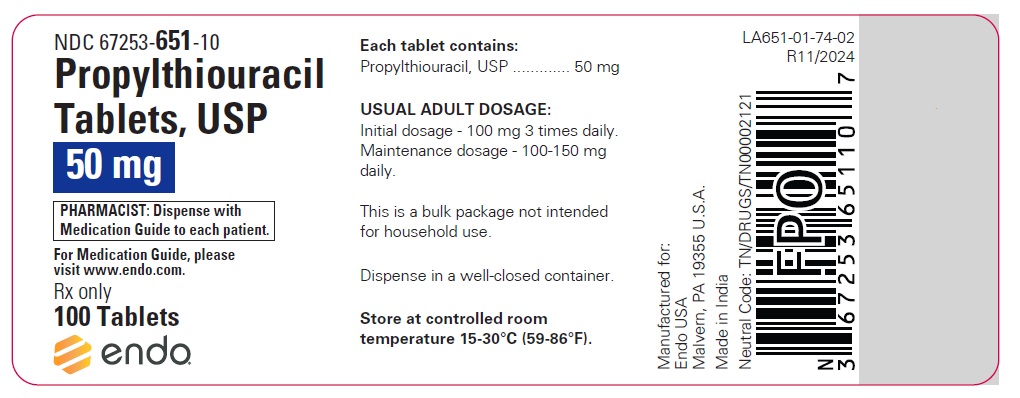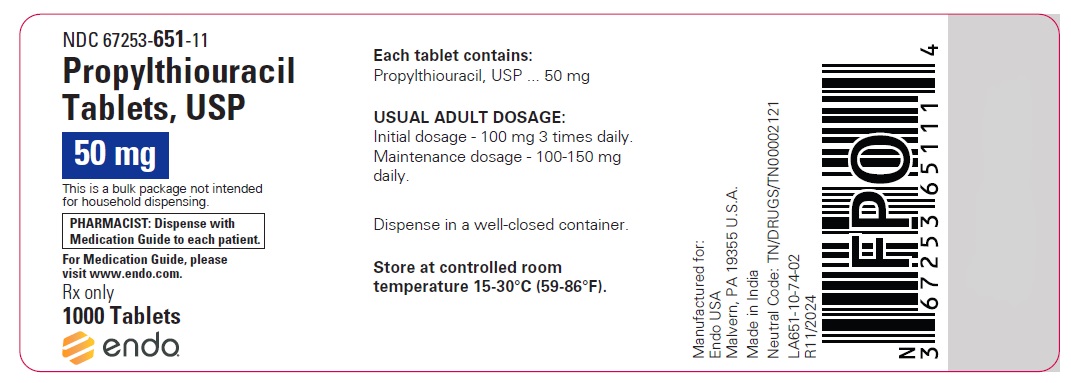 DRUG LABEL: Propylthiouracil
NDC: 67253-651 | Form: TABLET
Manufacturer: Endo USA, Inc.
Category: prescription | Type: HUMAN PRESCRIPTION DRUG LABEL
Date: 20241122

ACTIVE INGREDIENTS: PROPYLTHIOURACIL 50 mg/1 1
INACTIVE INGREDIENTS: CELLULOSE, MICROCRYSTALLINE; DOCUSATE SODIUM; MAGNESIUM STEARATE; SODIUM BENZOATE; SODIUM GLYCOLATE; STARCH, CORN

PROPYLTHIOURACIL TABLETS, USP

WARNING

Severe liver injury and acute liver failure, in some cases fatal, have been reported in patients treated with propylthiouracil. These reports of hepatic reactions include cases requiring liver transplantation in adult and pediatric patients.

Propylthiouracil should be reserved for patients who cannot tolerate methimazole and in whom radioactive iodine therapy or surgery are not appropriate treatments for the management of hyperthyroidism.
Propylthiouracil may be the treatment of choice when an antithyroid drug is indicated during or just prior to the first trimester of pregnancy (see Warnings and Precautions).

DESCRIPTION

Propylthiouracil is one of the thiocarbamide compounds. It is a white, crystalline substance that has a bitter taste and is very slightly soluble in water. Propylthiouracil is an antithyroid drug administered orally. The structural formula is:

Each tablet contains propylthiouracil 50 mg and the following inactive ingredients: corn starch, docusate sodium, magnesium stearate, microcrystalline cellulose, pregelatinized starch, sodium benzoate, and sodium starch glycolate.

CLINICAL PHARMACOLOGY

Propylthiouracil inhibits the synthesis of thyroid hormones and thus is effective in the treatment of hyperthyroidism. The drug does not inactivate existing thyroxine and triiodothyronine that are stored in the thyroid or circulating in the blood, nor does it interfere with the effectiveness of thyroid hormones given by mouth or by injection. Propylthiouracil inhibits the conversion of thyroxine to triiodothyronine in peripheral tissues and may therefore be an effective treatment for thyroid storm.

Propylthiouracil is readily absorbed and is extensively metabolized. Approximately 35% of the drug is excreted in the urine, in intact and conjugated forms, within 24 hours.

INDICATIONS AND USAGE

Propylthiouracil is indicated:

- in patients with Graves’ disease with hyperthyroidism or toxic multinodular goiter who are intolerant of methimazole and for whom surgery or radioactive iodine therapy is not an appropriate treatment option
- to ameliorate symptoms of hyperthyroidism in preparation for thyroidectomy or radioactive iodine therapy in patients who are intolerant of methimazole

CONTRAINDICATIONS

Propylthiouracil is contraindicated in patients who have demonstrated hypersensitivity to the drug or any of the other product components.

WARNINGS

Liver Toxicity

Liver injury resulting in liver failure, liver transplantation, or death, has been reported with propylthiouracil therapy in adult and pediatric patients. No cases of liver failure have been reported with the use of methimazole in pediatric patients. For this reason, propylthiouracil is not recommended for pediatric patients except when methimazole is not well-tolerated and surgery or radioactive iodine therapy are not appropriate therapies.

Biochemical monitoring of liver function (bilirubin, alkaline phosphatase) and hepatocellular integrity (ALT, AST) is not expected to attenuate the risk of severe liver injury due to its rapid and unpredictable onset. Patients should be informed of the risk of liver failure. Patients should be instructed to report any symptoms of hepatic dysfunction (anorexia, pruritus, right upper quadrant pain, etc.), particularly in the first six months of therapy. When these symptoms occur, propylthiouracil should be discontinued immediately and liver function tests and ALT and AST levels obtained.

Use in Pregnancy

There are cases of liver injury, including liver failure and death, in women treated with propylthiouracil during pregnancy. Two reports of in utero exposure with liver failure and death of a newborn have been reported. If propylthiouracil is used during pregnancy, or if the patient becomes pregnant while taking propylthiouracil, the patient should be warned of the rare potential hazard to the mother and fetus of liver damage.

Propylthiouracil crosses the placenta and can cause fetal goiter and cretinism when administered to a pregnant woman (see Precautions, Pregnancy).

After the first trimester of pregnancy, the use of an alternative antithyroid medication may be advisable (see Precautions, Pregnancy).

Agranulocytosis

Agranulocytosis occurs in approximately 0.2% to 0.5% of patients and is a potentially life-threatening side effect of propylthiouracil therapy. Agranulocytosis typically occurs within the first 3 months of therapy. Patients should be instructed to immediately report any symptoms suggestive of agranulocytosis, such as fever or sore throat. Leukopenia, thrombocytopenia, and aplastic anemia (pancytopenia) may also occur. Propylthiouracil should be discontinued if agranulocytosis, aplastic anemia (pancytopenia) is suspected, and the patient's bone marrow indices should be obtained.

Vasculitis

Cases of vasculitis resulting in severe complications and death have been reported in patients receiving propylthiouracil therapy. The cases of vasculitis include: glomerulonephritis, leukocytoclastic cutaneous vasculitis, alveolar/pulmonary hemorrhage, cerebral angiitis, and ischemic colitis. Most cases were associated with anti-neutrophilic cytoplasmic antibodies (ANCA)-positive vasculitis. In some cases, vasculitis resolved/improved with drug discontinuation; however, more severe cases required treatment with additional measures including corticosteroids, immunosuppressant therapy, and plasmapheresis. If vasculitis is suspected, discontinue therapy and initiate appropriate intervention.

Hypothyroidism

Propylthiouracil can cause hypothyroidism necessitating routine monitoring of TSH and free T4 levels with adjustments in dosing to maintain a euthyroid state. Because the drug readily crosses placental membranes, propylthiouracil can cause fetal goiter and cretinism when administered to a pregnant woman (see Precautions, Pregnancy).

PRECAUTIONS

General

Patients should be instructed to report any symptoms of hepatic dysfunction (anorexia, pruritus, jaundice, light colored stools, dark urine, right upper quadrant pain, etc.), particularly in the first six months of therapy. When these symptoms occur, measurement should be made of liver function (bilirubin, alkaline phosphatase) and hepatocellular integrity (ALT/AST levels).

Patients who receive propylthiouracil should be under close surveillance and should be counseled regarding the necessity of immediately reporting any evidence of illness, particularly sore throat, skin eruptions, fever, headache, or general malaise. In such cases, white blood cell and differential counts should be obtained to determine whether agranulocytosis has developed. Particular care should be exercised with patients who are receiving concomitant drugs known to be associated with agranulocytosis.

Information for Patients

Patients should be advised that if they become pregnant or intend to become pregnant while taking an antithyroid drug, they should contact their physician immediately about their therapy.

Patients should report immediately any evidence of illness, in particular sore throat, skin eruptions, fever, headache, or general malaise. They also should report symptoms suggestive of hepatic dysfunction (anorexia, pruritus, right upper quadrant pain, etc.).

Inform patients that cases of vasculitis resulting in severe complications and death have occurred with propylthiouracil. Inform patients to promptly report symptoms that may be associated with vasculitis including new rash, hematuria or decreased urine output, dyspnea or hemoptysis (see WARNINGS and ADVERSE REACTIONS).

Laboratory Tests

Because propylthiouracil may cause hypoprothrombinemia and bleeding, monitoring of prothrombin time should be considered during therapy with the drug, especially before surgical procedures.

Thyroid function tests should be monitored periodically during therapy. Once clinical evidence of hyperthyroidism has resolved, the finding of an elevated serum TSH indicates that a lower maintenance dose of propylthiouracil should be employed.

Drug Interactions

Anticoagulants (oral): Due to the potential inhibition of vitamin K activity by propylthiouracil, the activity of oral anticoagulants (e.g., warfarin) may be increased; additional monitoring of PT/INR should be considered, especially before surgical procedures.

Beta-adrenergic blocking agents: Hyperthyroidism may cause an increased clearance of beta blockers with a high extraction ratio. A reduced dose of beta-adrenergic blockers may be needed when a hyperthyroid patient becomes euthyroid.

Digitalis glycosides: Serum digitalis levels may be increased when hyperthyroid patients on a stable digitalis glycoside regimen become euthyroid; a reduced dose of digitalis glycosides may be needed.

Theophylline: Theophylline clearance may decrease when hyperthyroid patients on a stable theophylline regimen become euthyroid; a reduced dose of theophylline may be needed.

Carcinogenesis, Mutagenesis, Impairment of Fertility

Laboratory animals treated with propylthiouracil for >1 year have demonstrated thyroid hyperplasia and carcinoma formation. Such animal findings are seen with continuous suppression of thyroid function by sufficient doses of a variety of antithyroid agents, as well as in dietary iodine deficiency, subtotal thyroidectomy, and implantation of autonomous thyrotropic hormone-secreting pituitary tumors. Pituitary adenomas have also been described.

Pregnancy

Pregnancy Category D.

See WARNINGS.

In pregnant women with untreated or inadequately treated Graves’ disease, there is an increased risk of adverse events of maternal heart failure, spontaneous abortion, preterm birth, stillbirth and fetal or neonatal hyperthyroidism.

If propylthiouracil is used during pregnancy, or if the patient becomes pregnant while taking propylthiouracil, the patient should be warned of the rare potential hazard to the mother and fetus of liver damage.

Because propylthiouracil crosses placental membranes and can induce goiter and cretinism in the developing fetus, it is important that a sufficient, but not excessive, dose be given during pregnancy. In many pregnant women, the thyroid dysfunction diminishes as the pregnancy proceeds; consequently a reduction of dosage may be possible. In some instances, antithyroid therapy can be discontinued several weeks or months prior to delivery.

Since methimazole may be associated with the rare development of fetal abnormalities propylthiouracil may be the preferred agent during the first trimester of pregnancy. Given the potential for maternal hepatotoxicity from propylthiouracil, it may be preferable to switch from propylthiouracil to methimazole for the second and third trimesters during pregnancy.

Nursing Mothers

Propylthiouracil is present in breast milk to a small extent and therefore likely results in clinically insignificant doses to the nursing infant. In one study, nine lactating women were administered 400 mg of propylthiouracil by mouth. The mean amount of propylthiouracil excreted during 4 hours after drug administration was 0.025% of the administered dose.

Pediatric Use

Postmarketing reports of severe liver injury including hepatic failure requiring liver transplantation or resulting in death have been reported in the pediatric population (see WARNINGS). No such reports have been observed with methimazole. As such, propylthiouracil is not recommended for use in the pediatric population except in rare instances in which methimazole is not well-tolerated and surgery or radioactive iodine therapy are not appropriate.

When used in children, parents and patients should be informed of the risk of liver failure. If patients taking propylthiouracil develop tiredness, nausea, anorexia, fever, pharyngitis, or malaise, propylthiouracil should be discontinued immediately by the patient, a physician should be contacted, and a white blood cell count, liver function tests, and transaminase levels obtained.

ADVERSE REACTIONS

The following adverse reactions have been reported with the use of propylthiouracil. Because these events generally come from voluntary reporting from a population of uncertain size, it is not possible to reliably estimate their frequency or establish a causal relationship to drug exposure.

Severe adverse reactions include liver injury presenting as hepatitis, liver failure necessitating liver transplantation or resulting in death (see WARNINGS). Inhibition of myelopoiesis (agranulocytosis, granulopenia, aplastic anemia, and thrombocytopenia), drug fever, a lupus-like syndrome (including splenomegaly and vasculitis), periarteritis, hypoprothrombinemia, and bleeding have been reported. Nephritis, glomerulonephritis, interstitial pneumonitis, exfoliative dermatitis, and erythema nodosum have also been reported.

There are reports of a vasculitis associated with the presence of anti-neutrophilic cytoplasmic antibodies (ANCA), resulting in severe complications and death (see WARNINGS).

There have been rare reports of serious hypersensitivity reactions (e.g., Stevens Johnson syndrome and toxic epidermal necrolysis) in patients treated with propylthiouracil. Other adverse reactions include skin rash, uticaria, nausea, vomiting, epigastric distress, arthralgia, paresthesias, loss of taste, taste perversion, abnormal loss of hair, myalgia, headache, pruritus, drowsiness, neuritis, edema, vertigo, skin pigmentation, jaundice, sialadenopathy, and lymphadenopathy.

OVERDOSAGE

Signs and Symptoms

Nausea, vomiting, epigastric distress, headache, fever, arthralgia, pruritus, edema, and pancytopenia. Agranulocytosis is the most serious effect. Rarely, exfoliative dermatitis, hepatitis, neuropathies or CNS stimulation or depression may occur.

No information is available on the following: LD50; concentration of propylthiouracil in biologic fluids associated with toxicity and/or death; the amount of drug in a single dose usually associated with symptoms of overdosage; or the amount of propylthiouracil in a single dose likely to be life-threatening.

Treatment

To obtain up-to-date information about the treatment of overdose, a good resource is the certified Regional Poison Control Center. In managing overdosage, consider the possibility of multiple drug overdoses, interaction among drugs, and unusual drug kinetics in the patient.

In the event of an overdose, appropriate supportive treatment should be initiated as dictated by the patient’s medical status.

DOSAGE AND ADMINISTRATION

Propylthiouracil is administered orally. The total daily dosage is usually given in 3 equal doses at approximately 8-hour intervals.

Adults

The initial dose is 300 mg daily. In patients with severe hyperthyroidism, very large goiters, or both, the initial dose may be increased to 400 mg daily; an occasional patient will require 600 to 900 mg daily initially. The usual maintenance dose is 100 to 150 mg daily.

Pediatric Patients

Propylthiouracil is generally not recommended for use in the pediatric patient population except in rare instances in which other alternative therapies are not appropriate options. Studies evaluating appropriate dosing regimen have not been conducted in the pediatric population although general practice would suggest initiation of therapy in patients 6 years or older at a dosage of 50 mg daily with careful upward titration based on clinical response and evaluation of TSH and free T4 levels. Although cases of severe liver injury have been reported with doses as low as 50 mg/day, most cases were associated with doses of 300 mg/day and higher.

Geriatric Patients

Clinical studies of propylthiouracil did not include sufficient numbers of subjects aged 65 or over to determine whether they respond differently from younger subjects. Other reported clinical experience has not identified differences in responses between the elderly and younger patients.

In general, dose selection for an elderly patient should be cautious reflecting the greater frequency of decreased hepatic, renal, or cardiac function, and of concomitant disease or other drug therapy.

HOW SUPPLIED

Propylthiouracil Tablets, USP, 50 mg, are round, white, scored tablets, engraved P33, supplied as:

NDC 67253-651-10 Bottle of 100
NDC 67253-651-11 Bottle of 1000

Store at controlled room temperature 15°-30°C (59°-86°F).

REFERENCE

- International Agency for Research on Cancer. IARC Monographs on the Evaluation of the Carcinogenic Risk of Chemicals to Man. 1974; 7; 67-76.

For more information, call 1-800-828-9393.

For Medication Guide, please visit www.endo.com.

Manufactured for:

Endo USA

Malvern, PA 19355 U.S.A.

Made in India

Neutral Code: TN/DRUGS/TN00002121

© 2024 Endo, Inc. or one of its affiliates.

OS651-01-74-02

Revised: 11/2024

MEDICATION GUIDE

PROPYLTHIOURACIL (Pro-pil-thi-o-ur-a-sil) Tablets

Read this Medication Guide before you start taking Propylthiouracil and each time you get a refill. There may be new information. This Medication Guide does not take the place of talking to your doctor about your medical condition or treatment.

What is the most important information I should know about Propylthiouracil?

Propylthiouracil can cause serious side effects, including:

- Severe liver problems. In some cases, liver problems can happen in people who take Propylthiouracil including: liver failure, the need for liver transplant, or death. Stop taking Propylthiouracil and call your doctor right away if you have any of these symptoms:
  - fever
  - loss of appetite
  - nausea
  - vomiting
  - tiredness
  - itchiness
  - pain or tenderness in your right upper stomach area (abdomen)
  - dark (tea colored) urine
  - pale or light colored bowel movements (stools)
  - yellowing of your skin or whites of your eyes
- Serious risks during pregnancy. Propylthiouracil may cause liver problems, liver failure and death in pregnant women and may harm your unborn baby. Propylthiouracil may also cause liver problems or death of infants born to women who take Propylthiouracil during certain trimesters of pregnancy. Propylthiouracil may be used when an antithyroid drug is needed during or just before the first trimester of pregnancy.

If you get pregnant while taking Propylthiouracil, call your doctor right away about your therapy.

What is Propylthiouracil?

Propylthiouracil is a prescription medicine used to treat people who have Graves’ disease with hyperthyroidism or toxic multinodular goiter. Propylthiouracil is used when:

- certain other antithyroid medicines do not work well.
- thyroid surgery or radioactive iodine therapy is not a treatment option.
- to decrease symptoms of hyperthyroidism in preparation for a thyroidectomy (removal of the thyroid gland) or radioactive iodine therapy.

Propylthiouracil is not recommended for use in children.

Who should not take Propylthiouracil?

Do not take Propylthiouracil if you are allergic to Propylthiouracil or any of its ingredients. See the end of this Medication Guide for a complete list of ingredients in Propylthiouracil.

What should I tell my doctor before taking Propylthiouracil?

Before you take Propylthiouracil, tell your doctor if you:

- plan to have surgery.
- have any other medical conditions
- are pregnant or plan to become pregnant. Talk to your doctor right away if you are pregnant or plan to become pregnant. Propylthiouracil may harm or cause death of your unborn baby.
- are breast-feeding or plan to breast-feed. Propylthiouracil can pass into your breast milk. Talk to your doctor about the best way to feed your baby if you take Propylthiouracil.

Tell your doctor about all the medicines you take, including prescription and over-the-counter medicines, vitamins, and herbal supplements. Propylthiouracil may affect the way other medicines work.

Especially, tell your doctor if you take:

- a blood thinner medicine warfarin sodium (Coumadin, Jantoven)
- medicine for heart problems
- medicine for high blood pressure
- Digoxin (Lanoxicaps, Lanoxin)
- Theophylline (Elixophyllin, Theolair, Theochron, Theo-24, Uniphyl)

Ask your doctor if you are not sure if your medicine is one of these.

Know the medicines you take. Keep a list of them to show your doctor and pharmacist when you get a new medicine.

How should I take Propylthiouracil?

- Take Propylthiouracil exactly as your doctor tells you to take it.
- Your doctor may change your dose if needed.
- Propylthiouracil is usually taken 3 times a day (every 8 hours).
- If you take too much Propylthiouracil, call your Poison Control Center at 1-800-222-1222 or go to the nearest hospital emergency room right away.
  - If you take too much Propylthiouracil you may have the following symptoms: nausea, vomiting, upper stomach pain or tenderness, headache, fever, joint pain, and swelling of your body, arms, and legs.
- If you miss a dose of Propylthiouracil, take it as soon as you remember. If it is almost time for your next dose, skip the missed dose. Just take the next dose at your regular time. Do not double your dose.

What should I avoid while taking Propylthiouracil?

Propylthiouracil can cause dizziness, drowsiness or sleepiness. If you have these symptoms do not drive, operate machinery, or do other dangerous activities until you know how Propylthiouracil affects you.

What are the possible side effects of Propylthiouracil?

Propylthiouracil may cause serious side effects, including:

- See “What is the most important information I should know about Propylthiouracil?”
- Low white blood cell counts.
  - This usually happens within the first 3 months of treatment and can be life-threatening. You may have a higher chance of getting an infection when your white blood cell count is low.
  - Call your doctor right away if you have symptoms of infection or illness such as fever, chills, or sore throat.
- Swelling (inflammation) of the small blood vessels of the body (vasculitis). Some people have developed vasculitis, a serious complication, during their treatment with Propylthiouracil that can lead to death. Vasculitis can involve the small blood vessels of the skin, kidneys, or lungs. Symptoms may vary depending on which blood vessels are affected. Tell your healthcare provider right away if you develop changes in your:
  - skin, such as red or purple changes in color, a rash, pain, or swelling,
  - urine, such as pink or dark in color, looks foamy, decrease in the amount produced, or
  - breathing, such as shortness of breath or coughing up blood.
- Increased risk of bleeding. You may have increased bleeding especially if you have surgery or if you are taking blood thinners.
- Hypothyroidism (low thyroid problems). Your doctor should do blood tests regularly during treatment to check your thyroid.
- Severe skin reactions (Stevens Johnson syndrome). Propylthiouracil may cause rare, but serious skin reactions that may require stopping its use. This may need to be treated in a hospital and may be life-threatening. Call your doctor right away or get emergency help if you have skin blisters, peeling rash, sores in the mouth, hives or any other allergic reactions.

The most common side effects of Propylthiouracil include:

- nausea
- vomiting
- upper stomach pain or tenderness
- joint pain
- itching or tingling
- loss or change in taste
- loss of hair
- muscle pain
- headache
- sleepiness
- nerve pain
- swelling (edema)
- dizziness
- enlarged salivary glands or enlarged lymph nodes

Tell your doctor if you have any side effect that bothers you or that does not go away.

These are not all of the possible side effects of Propylthiouracil. For more information, ask your doctor or pharmacist.

Call your doctor for medical advice about side effects. You may report side effects to FDA at 1-800-FDA-1088.

How should I store Propylthiouracil?

- Store Propylthiouracil at room temperature between 15° to 30°C (59° to 86°F).

Keep Propylthiouracil and all medicines out of the reach of children.

General information about the safe and effective use of Propylthiouracil.

Medicines are sometimes prescribed for purposes other than those listed in a Medication Guide. Do not use Propylthiouracil for a condition for which it was not prescribed. Do not give Propylthiouracil to other people, even if they have the same symptoms that you have. It may harm them.

This Medication Guide summarizes the most important information about Propylthiouracil. If you would like more information, talk with your doctor. You can ask your pharmacist or doctor for information about Propylthiouracil that is written for health professionals.

For more information call 1-800-828-9393.

What are the ingredients in Propylthiouracil?

Active ingredient: propylthiouracil
Inactive ingredients: corn starch, docusate sodium, magnesium stearate, microcrystalline cellulose, pregelatinized starch, sodium benzoate, and sodium starch glycolate.

For Medication Guide, please visit www.endo.com.

Rx only

Manufactured for:

Endo USA

Malvern, PA 19355 U.S.A.

Made in India

Neutral Code: TN/DRUGS/TN00002121

© 2024 Endo, Inc. or one of its affiliates.

PD651-01-74-02

Revised: 11/2024

This Medication Guide has been approved by the U.S. Food and Drug Administration